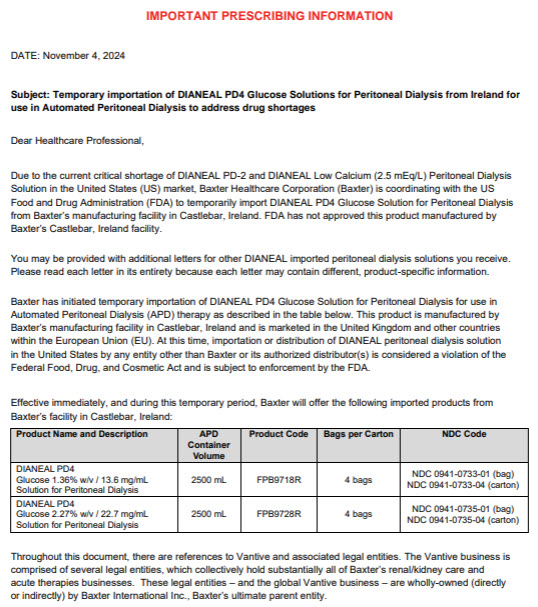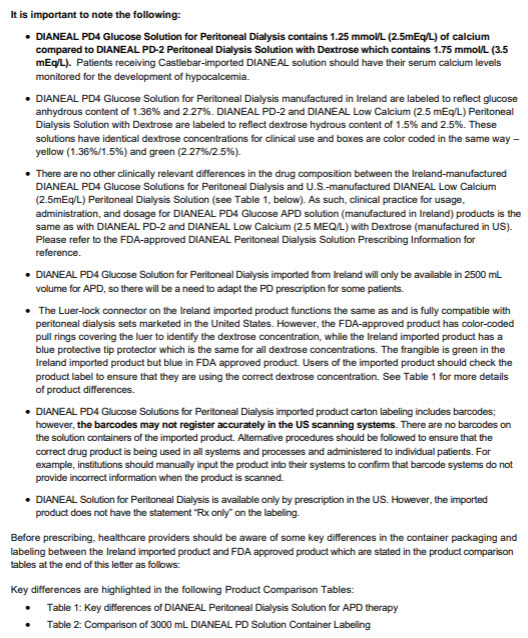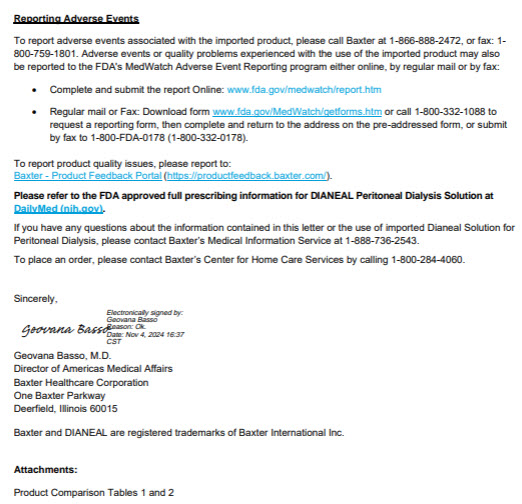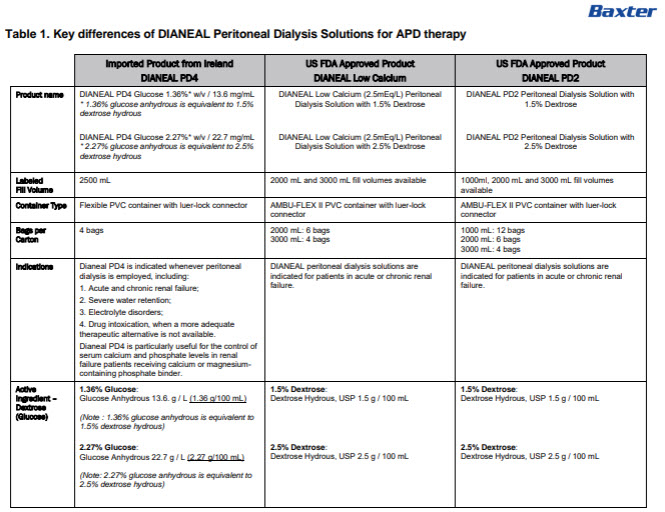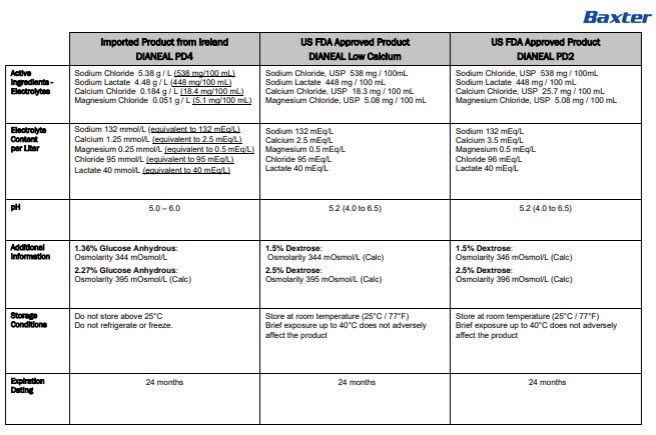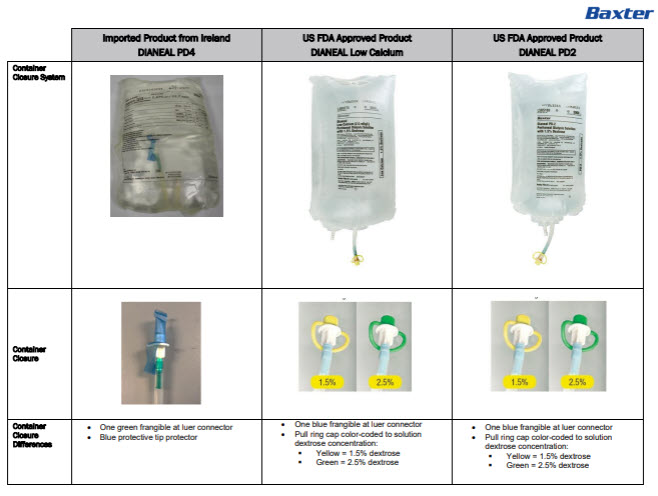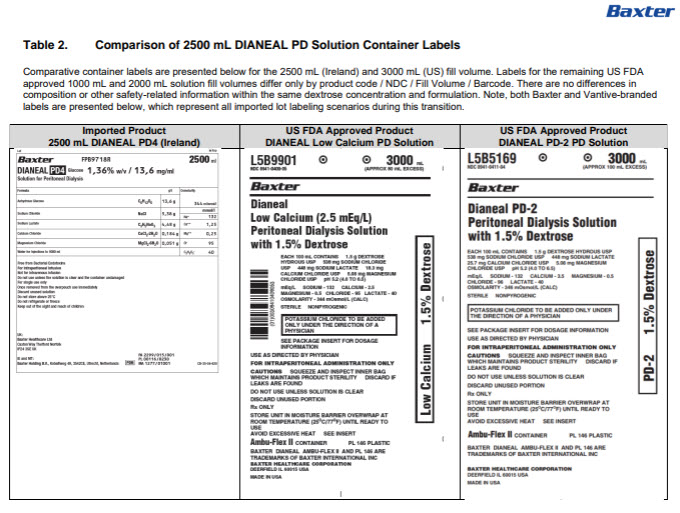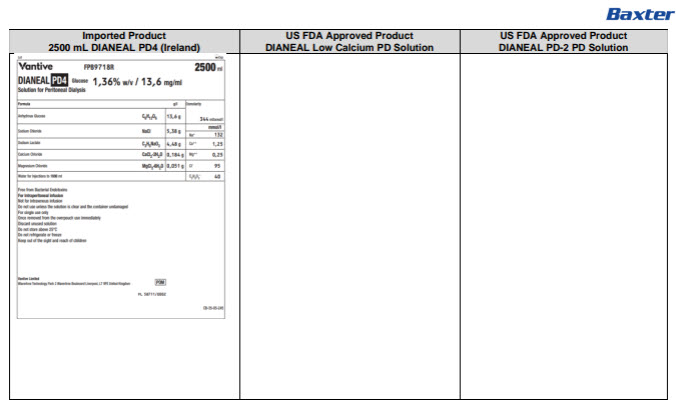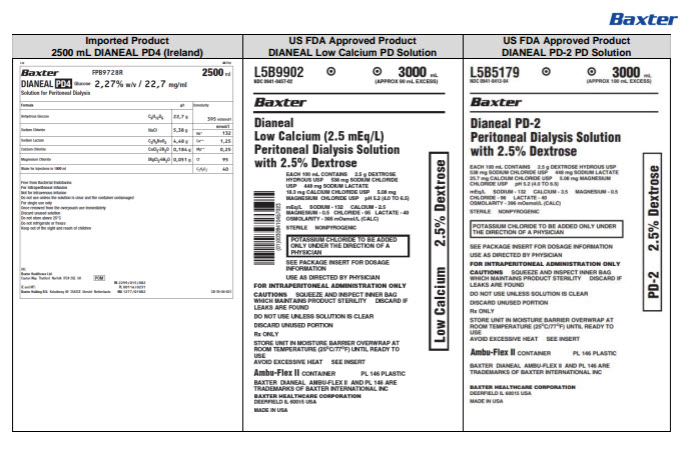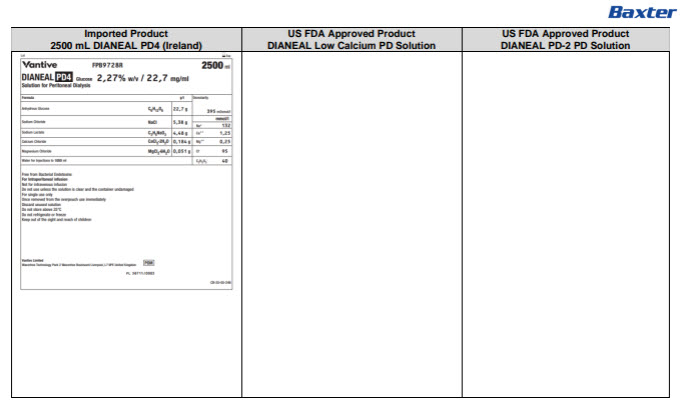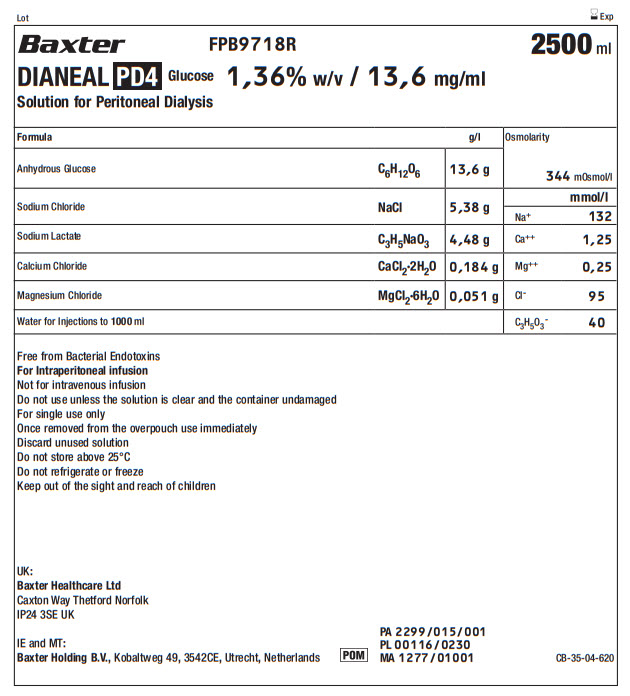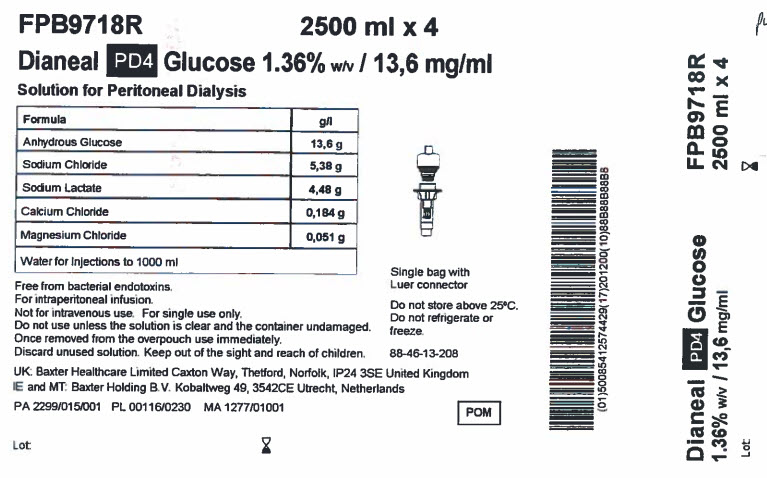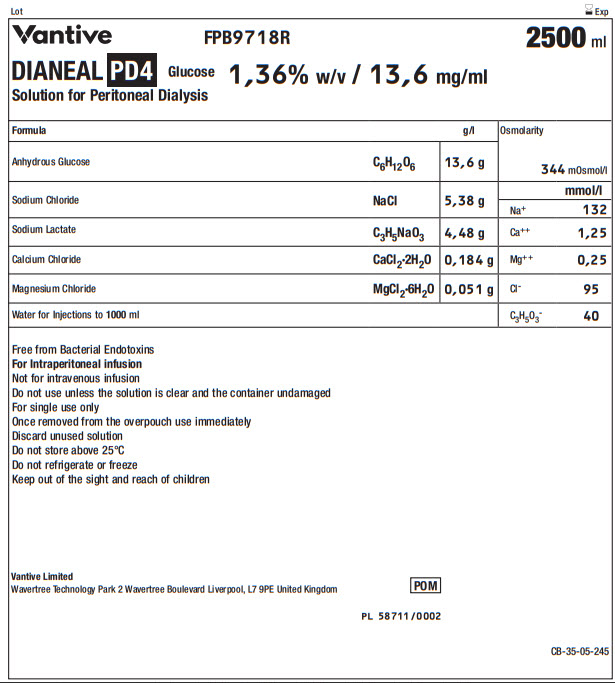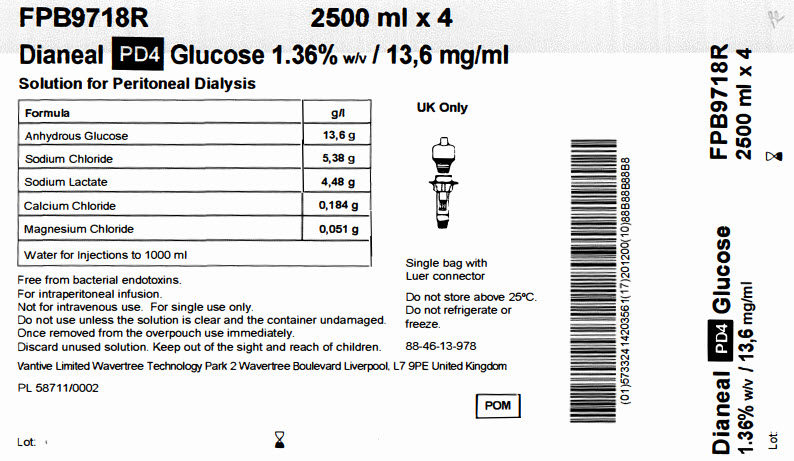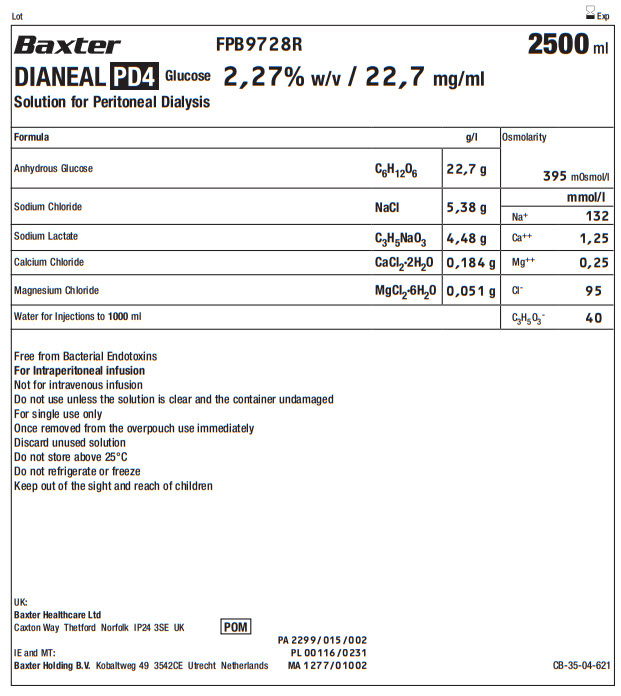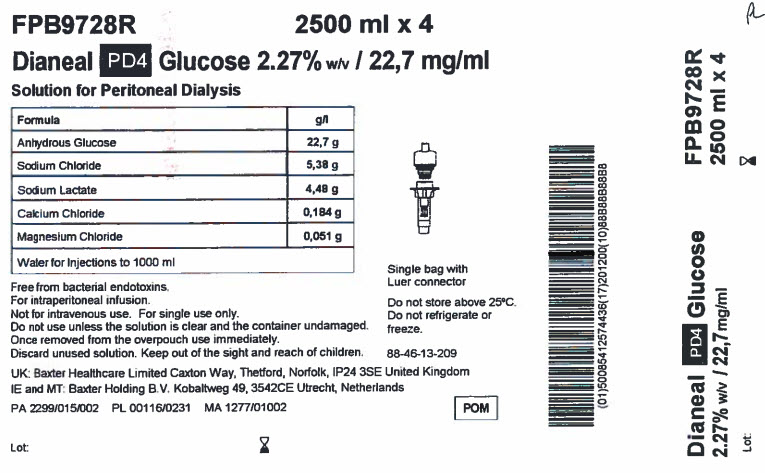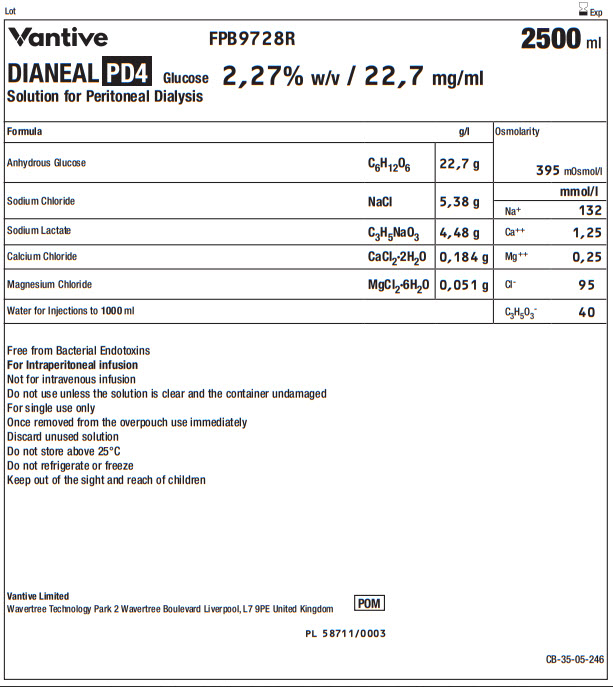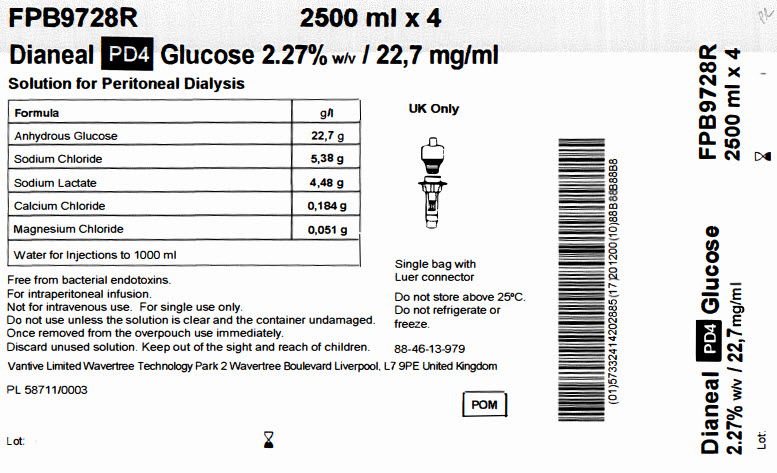 DRUG LABEL: DIANEAL LOW CALCIUM WITH DEXTROSE
NDC: 0941-0733 | Form: INJECTION, SOLUTION
Manufacturer: Vantive US Healthcare LLC
Category: prescription | Type: HUMAN PRESCRIPTION DRUG LABEL
Date: 20250702

ACTIVE INGREDIENTS: DEXTROSE MONOHYDRATE 1.36 g/100 mL; SODIUM CHLORIDE 538 mg/100 mL; SODIUM LACTATE 448 mg/100 mL; CALCIUM CHLORIDE 18.4 mg/100 mL; MAGNESIUM CHLORIDE 5.1 mg/100 mL

DIANEAL Low Calcium with Dextrose

PACKAGE/LABEL PRINCIPAL DISPLAY PANEL

Lot Exp

BaxterLogo FPB9718R 2500 ml

DIANEAL PD4 Glucose 1,36% w/v / 13,6 mg/ml

Solution for Peritoneal Dialysis

Formula |  | g/l | Osmolarity | 344mOsmol/l
Anhydrous Glucose | C6H12O6 | 13,6 g |  | mmol/l
Sodium Chloride | NaCl | 5,38 g | Na^+ | 1. 132
Sodium Lactate | C3H5NaO3 | 4,48 g | Ca^++ | 1,25
Calcium Chloride | CaCl2·2H2O | 0,184 g | Mg^++ | 0,25
Magnesium Chloride | MgCl2·6H2O | 0,051 g | Cl^- | 95
Water for Injections to 1000ml |  |  | C3H5O3^- | 40

Free from Bacterial Endotoxins
For Intraperitoneal infusion
Not for intravenous infusion
Do not use unless the solution is clear and the container undamaged
For single use only
Once removed from the overpouch use immediately
Discard unused solution
Do not store above 25°C
Do not refrigerate or freeze
Keep out of the sight and reach of children

UK:
Baxter Healthcare Ltd
Caxton Way Thetford Norfolk
IP24 3SE UK

IE and MT:
Baxter Holding B.V., Kobaltweg 49, 3542CE, Utrecht, Netherlands

POM Symbol

PA 2299/015/001
PL 00116/0230
MA 1277/01001

CB-35-04-620

FPB9718R 2500 ml x 4

Dianeal PD4 Glucose 1.36% w/v / 13,6 mg/ml

Solution for Peritoneal Dialysis

Formula | g/l
Anhydrous Glucose | 13,6 g
Sodium Chloride | 5,38 g
Sodium Lactate | 4,48 g
Calcium Chloride | 0,184 g
Magnesium Chloride | 0,051 g
Water for Injections to 1000 ml

Free from bacterial endotoxins.
For intraperitoneal infusion.
Not for intravenous use. For single use only.
Do not use unless the solution is clear and the container undamaged.
Once removed from the overpouch use immediately.
Discard unused solution. Keep out of the sight and reach of children.

UK: Baxter Healthcare Limited Caxton Way, Thetford, Norfolk, IP24 3SE United Kingdom

IE and MT: Baxter Holding B.V. Kobaltweg 49, 3542CE Utrecht, Netherlands

PA 2299/015/001 PL 00116/0230 MA 1277/01001

POM Symbol

Lot:

Single bag with
Luer connector

Do not store above 25°C.
Do not refrigerate or
freeze.

88-46-13-208

Barcode
(01)50085412574429(17)201200(10)88B88B88B8

Dianeal PD4 Glucose FPB9718R

1.36% w/v / 13,6 mg/ml 2500 ml x 4

Lot:

Lot Exp

Vantive Logo FPB9718R 2500 ml

DIANEAL PD4 Glucose 1,36% w/v / 13,6 mg/ml

Solution for Peritoneal Dialysis

Formula |  | g/l | Osmolarity | 344mOsmol/l
Anhydrous Glucose | C6H12O6 | 13,6 g |  | mmol/l
Sodium Chloride | NaCl | 5,38 g | Na^+ | 1. 132
Sodium Lactate | C3H5NaO3 | 4,48 g | Ca^++ | 1,25
Calcium Chloride | CaCl2·2H2O | 0,184 g | Mg^++ | 0,25
Magnesium Chloride | MgCl2·6H2O | 0,051 g | Cl^- | 95
Water for Injections to 1000ml |  |  | C3H5O3^- | 40

Free from Bacterial Endotoxins
For Intraperitoneal infusion
Not for intravenous infusion
Do not use unless the solution is clear and the container undamaged
For single use only
Once removed from the overpouch use immediately
Discard unused solution
Do not store above 25°C
Do not refrigerate or freeze
Keep out of the sight and reach of children

Vantive Limited
Wavertree Technology Park 2 Wavertree Boulevard Liverpool, L7 9PE United Kingdom

POM Symbol

PL 58711/0002

CB-35-05-245

FPB9718R 2500 ml x 4

Dianeal PD4 Glucose 1.36% w/v / 13,6 mg/ml

Solution for Peritoneal Dialysis

Formula | g/l
Anhydrous Glucose | 13,6 g
Sodium Chloride | 5,38 g
Sodium Lactate | 4,48 g
Calcium Chloride | 0,184 g
Magnesium Chloride | 0,051 g
Water for Injections to 1000 ml

Free from bacterial endotoxins.
For intraperitoneal infusion.
Not for intravenous use. For single use only.
Do not use unless the solution is clear and the container undamaged.
Once removed from the overpouch use immediately.
Discard unused solution. Keep out of the sight and reach of children.

Vantive Limited Wavertree Technology Park 2 Wavertree Boulevard Liverpool, L7 9PE United Kingdom

PL 58711/0002

POM Symbol

Lot:

UK Only

Single bag with
Luer connector

Do not store above 25°C.
Do not refrigerate or
freeze.

88-46-13-978

Barcode
(01)57332414203561(17)201200(10)88B88B88B8

Dianeal PD4 Glucose FPB9718R

1.36% w/v / 13,6 mg/ml 2500 ml x 4

Lot:

Lot Exp

BaxterLogo FPB9728R 2500 ml

DIANEAL PD4 Glucose 2,27% w/v / 22,7 mg/ml

Solution for Peritoneal Dialysis

Formula |  | g/l | Osmolarity | 395mOsmol/l
Anhydrous Glucose | C6H12O6 | 22,7 g |  | mmol/l
Sodium Chloride | NaCl | 5,38 g | Na^+ | 1. 132
Sodium Lactate | C3H5NaO3 | 4,48 g | Ca^++ | 1,25
Calcium Chloride | CaCl2·2H2O | 0,184 g | Mg^++ | 0,25
Magnesium Chloride | MgCl2·6H2O | 0,051 g | Cl^- | 95
Water for Injections to 1000ml |  |  | C3H5O3^- | 40

Free from Bacterial Endotoxins
For Intraperitoneal infusion
Not for intravenous infusion
Do not use unless the solution is clear and the container undamaged
For single use only
Once removed from the overpouch use immediately
Discard unused solution
Do not store above 25°C
Do not refrigerate or freeze
Keep out of the sight and reach of children

UK:
Baxter Healthcare Ltd
Caxton Way Thetford Norfolk IP24 3SE UK

IE and MT:
Baxter Holding B.V. Kobaltweg 49 3542CE Utrecht, Netherlands

POM Symbol

PA 2299/015/002
PL 00116/0231
MA 1277/01002

CB-35-04-621

FPB9728R 2500 ml x 4

Dianeal PD4 Glucose 2.27% w/v / 22,7 mg/ml

Solution for Peritoneal Dialysis

Formula | g/l
Anhydrous Glucose | 22,7 g
Sodium Chloride | 5,38 g
Sodium Lactate | 4,48 g
Calcium Chloride | 0,184 g
Magnesium Chloride | 0,051 g
Water for Injections to 1000 ml

Free from bacterial endotoxins.
For intraperitoneal infusion.
Not for intravenous use. For single use only.
Do not use unless the solution is clear and the container undamaged.
Once removed from the overpouch use immediately.
Discard unused solution. Keep out of the sight and reach of children.

UK: Baxter Healthcare Limited Caxton Way, Thetford, Norfolk, IP24 3SE United Kingdom

IE and MT: Baxter Holding B.V. Kobaltweg 49, 3542CE Utrecht, Netherlands

PA 2299/015/002 PL 00116/0231 MA 1277/01002

POM Symbol

Lot:

Single bag with
Luer connector

Do not store above 25°C.
Do not refrigerate or
freeze.

88-46-13-209

Barcode
(01)50085412574436(17)201200(10)88B88B88B8

Dianeal PD4 Glucose FPB9728R

2.27% w/v / 22,7 mg/ml 2500 ml x 4

Lot:

Lot Exp

Vantive Logo FPB9728R 2500 ml

DIANEAL PD4 Glucose 2,27% w/v / 22,7 mg/ml

Solution for Peritoneal Dialysis

Formula |  | g/l | Osmolarity | 395mOsmol/l
Anhydrous Glucose | C6H12O6 | 22,7 g |  | mmol/l
Sodium Chloride | NaCl | 5,38 g | Na^+ | 1. 132
Sodium Lactate | C3H5NaO3 | 4,48 g | Ca^++ | 1,25
Calcium Chloride | CaCl2·2H2O | 0,184 g | Mg^++ | 0,25
Magnesium Chloride | MgCl2·6H2O | 0,051 g | Cl^- | 95
Water for Injections to 1000ml |  |  | C3H5O3^- | 40

Free from Bacterial Endotoxins
For Intraperitoneal infusion
Not for intravenous infusion
Do not use unless the solution is clear and the container undamaged
For single use only
Once removed from the overpouch use immediately
Discard unused solution
Do not store above 25°C
Do not refrigerate or freeze
Keep out of the sight and reach of children

Vantive Limited
Wavertree Technology Park 2 Wavertree Boulevard Liverpool, L7 9PE United Kingdom

POM Symbol

PL 58711/0003

CB-35-05-246

FPB9728R 2500 ml x 4

Dianeal PD4 Glucose 2.27% w/v / 22,7 mg/ml

Solution for Peritoneal Dialysis

Formula | g/l
Anhydrous Glucose | 22,7 g
Sodium Chloride | 5,38 g
Sodium Lactate | 4,48 g
Calcium Chloride | 0,184 g
Magnesium Chloride | 0,051 g
Water for Injections to 1000 ml

Free from bacterial endotoxins.
For intraperitoneal infusion.
Not for intravenous use. For single use only.
Do not use unless the solution is clear and the container undamaged.
Once removed from the overpouch use immediately.
Discard unused solution. Keep out of the sight and reach of children.

Vantive Limited Wavertree Technology Park 2 Wavertree Boulevard Liverpool, L7 9PE United Kingdom

PL 58711/0003

POM Symbol

Lot:

UK Only

Single bag with
Luer connector

Do not store above 25°C.
Do not refrigerate or
freeze.

88-46-13-979

Barcode
(01)5733241420885(17)201200(10)88B88B88B8

Dianeal PD4 Glucose FPB9728R

2.27% w/v / 22,7 mg/ml 2500 ml x 4

Lot: